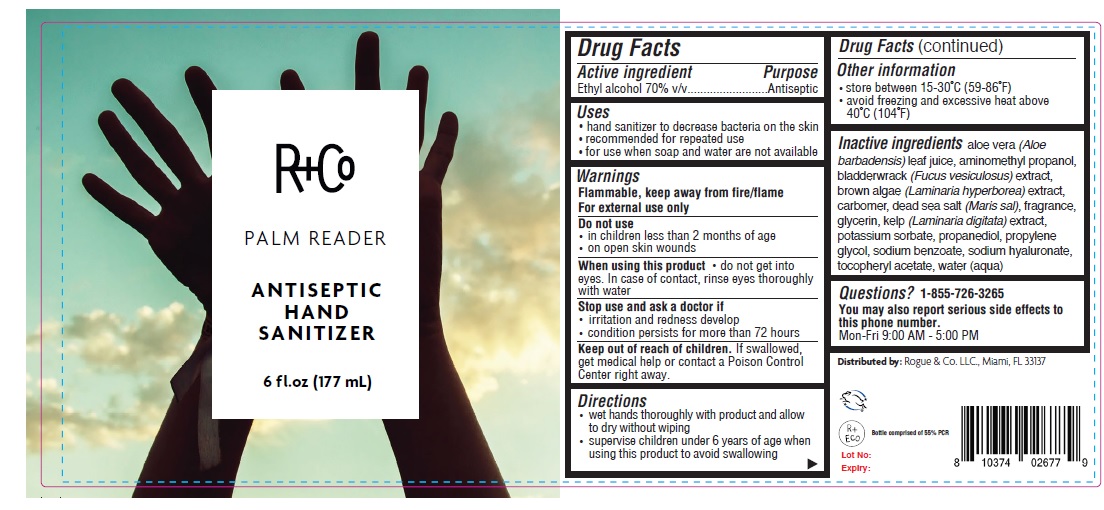 DRUG LABEL: R and Co PALM READER ANTISEPTIC HAND SANITIZER
NDC: 57367-202 | Form: GEL
Manufacturer: 220 Laboratories Inc.
Category: otc | Type: HUMAN OTC DRUG LABEL
Date: 20220225

ACTIVE INGREDIENTS: ALCOHOL 70 mL/100 mL
INACTIVE INGREDIENTS: ALOE VERA LEAF; AMINOMETHYLPROPANOL; FUCUS VESICULOSUS; LAMINARIA HYPERBOREA; CARBOMER HOMOPOLYMER, UNSPECIFIED TYPE; SEA SALT; GLYCERIN; LAMINARIA DIGITATA; POTASSIUM SORBATE; PROPANEDIOL; PROPYLENE GLYCOL; SODIUM BENZOATE; HYALURONATE SODIUM; .ALPHA.-TOCOPHEROL ACETATE; WATER

R and Co ANTISEPTIC HAND SANITIZER

Active ingredient

Ethyl alcohol 70% v/v

Purpose

Antiseptic

Uses

• hand sanitizer to decrease bacteria on the skin
• recommended for repeated use
• for use when soap and water are not available

Warnings

Flammable, keep away from fire/flame
For external use only

Do not use

• in children less than 2 months of age
• on open skin wounds

When using this product • do not get into eyes. In case of contact, rinse eyes thoroughly with water

Stop use and ask a doctor if
• irritation and redness develop
• condition persists for more than 72 hours

Keep out of reach of children. If swallowed, get medical help or contact a Poison Control Center right away.

Directions

• wet hands thoroughly with product and allow to dry without wiping
• supervise children under 6 years of age when using this product to avoid swallowing

Other information

• store between 15-30˚C (59-86˚F)

• avoid freezing and excessive heat above 40˚C (104˚F)

Inactive ingredients

aloe vera (Aloe barbadensis) leaf juice, aminomethyl propanol, bladderwrack (Fucus vesiculosus) extract, brown algae (Laminaria hyperborea) extract, carbomer, dead sea salt (Maris sal), fragrance, glycerin, kelp (Laminaria digitata) extract, potassium sorbate, propanediol, propylene glycol, sodium benzoate, sodium hyaluronate, tocopheryl acetate, water (aqua)

Questions? 1-855-726-3265

You may also report serious side effects to this phone number.

Mon-Fri 9:00 AM - 5:00 PM

PALM READER

Distributed by: Rogue & Co. LLC., Miami, FL 33137

Bottle comprised of 55% PCR

Lot No:
Expiry: